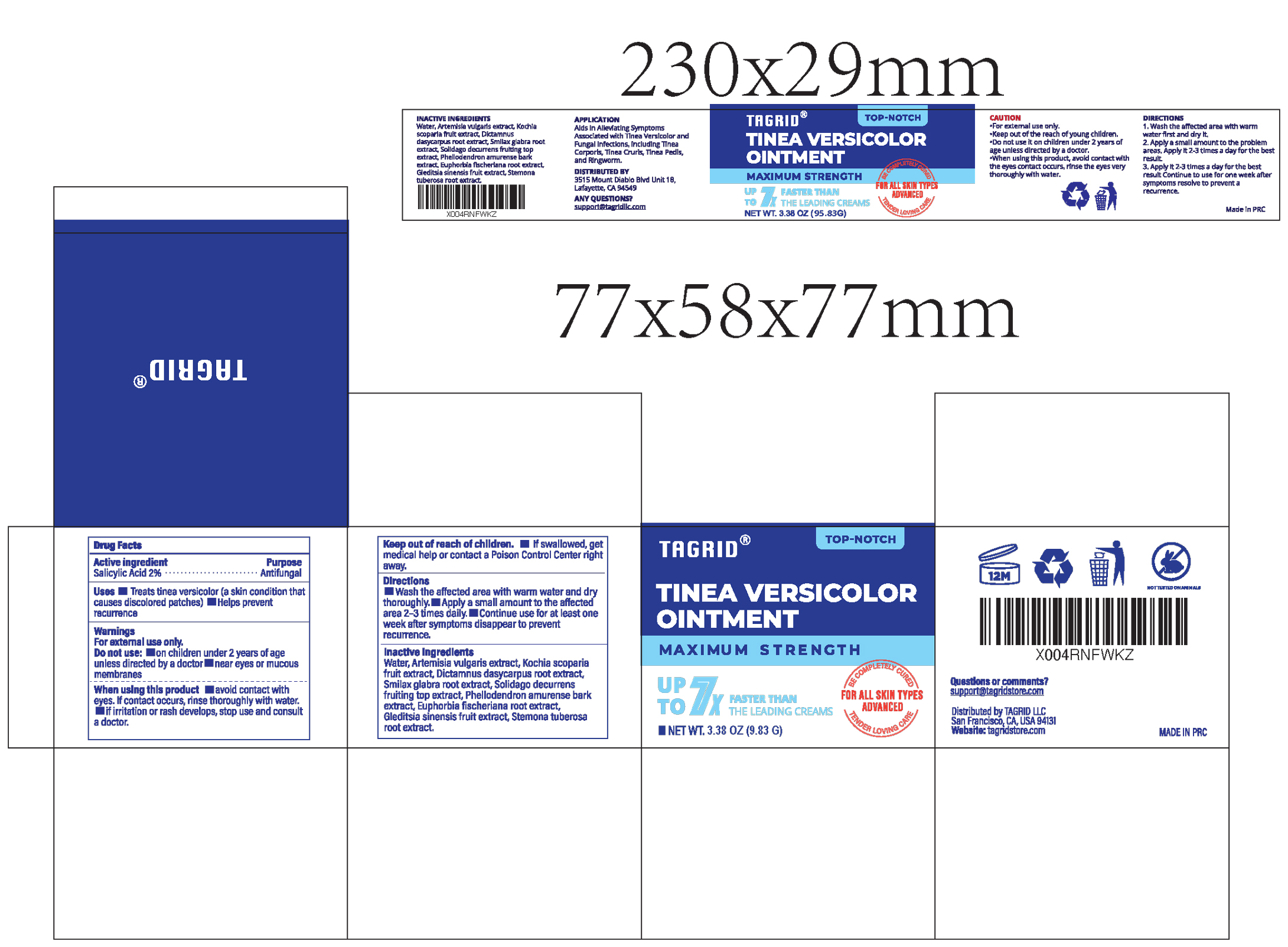 DRUG LABEL: TAGRID TINEA VERSICOLOR
NDC: 85384-0016 | Form: CREAM
Manufacturer: TAGRID LLC
Category: otc | Type: HUMAN OTC DRUG LABEL
Date: 20250719

ACTIVE INGREDIENTS: Salicylic Acid 2 g/100 g
INACTIVE INGREDIENTS: WATER; ARTEMISIA VULGARIS ROOT; BASSIA SCOPARIA FRUIT; DICTAMNUS DASYCARPUS ROOT; SMILAX GLABRA TUBER; SOLIDAGO DECURRENS FRUITING TOP; PHELLODENDRON AMURENSE BARK; EUPHORBIA FISCHERIANA ROOT; GLEDITSIA SINENSIS FRUIT; STEMONA TUBEROSA ROOT

Active ingredient:

1. Salicylic Acid 2%

PURPOSE

1. Antifungal

Uses:

1. Treats tinea versicolor (a skin condition that causes discolored patches)
2. Helps prevent recurrence

WARNINGS

For external use only

Do not use:

- on children under 2 years of age unless directed by a doctor
- near eyes or mucous membranes

When using this product

- avoid contact with eyes. If contact occurs, rinse thoroughly with water.
- if irritation or rash develops, stop use and consult a doctor.

Stop use and ask a doctor if

- If irritation or rash develops, stop use and consult a doctor.

Keep out of reach of children.

If swallowed, get medical help or contact a Poison Control Center right away.

Directions:

- Wash the affected area with warm water and dry thoroughly.
- Apply a small amount to the affected area 2–3 times daily.
- Continue use for at least one week after symptoms disappear to prevent recurrence.

Inactive ingredients:

- Water
- Artemisia vulgaris extract
- Kochia scoparia fruit extract
- Dictamnus dasycarpus root extract
- Smilax glabra root extract
- Solidago decurrens fruiting top extract
- Phellodendron amurense bark extract
- Euphorbia fischeriana root extract
- Gleditsia sinensis fruit extract
- Stemona tuberosa root extract

Questions or comments?

Contact us at support@tagridstore.com